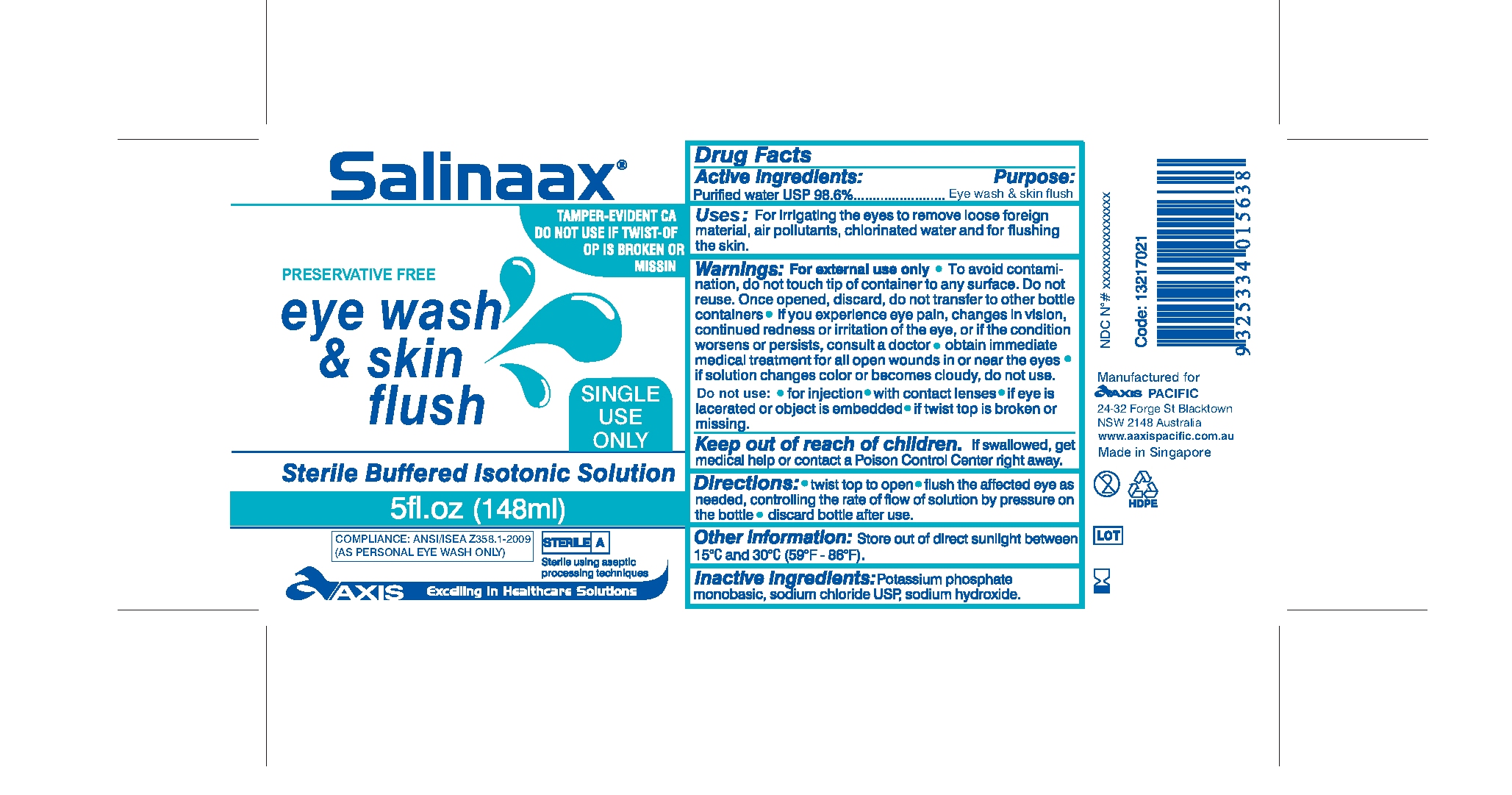 DRUG LABEL: Salinaax
NDC: 68276-005 | Form: RINSE
Manufacturer: Aaxis Pacific
Category: otc | Type: HUMAN OTC DRUG LABEL
Date: 20110311

ACTIVE INGREDIENTS: Water 98.6 mL/100 mL
INACTIVE INGREDIENTS: Potassium phosphate, monobasic; Sodium chloride; Sodium hydroxide

Active Ingredients:
Purified water USP 98.6%

Purpose:
Eye wash and skin flush

INDICATIONS AND USAGE

Uses: For irrigating the eyes to remove loose foreign material, air pollutants, chlorinated water and for flushing the skin.

WARNINGS

Warnings: For external use only. To avoid contamination, do not touch tip of container to any surface. Do not reuse. Once opened, discard, do not transfer to other bottle containers. If you experience eye pain, changes in vision, continued redness or irritation of the eye, or if the condition worsens or persists, consult a doctor, obtain immediate medical treatment for all open wounds in or near the eyes. If solution changes color or becomes cloudy, do not use.

Do Not Use:For injection, with contact lenses, If eye is lacerated or object is embedded, If twist top is broken or missing.

STOP USE

If solution changes color or becomes cloud, do not use.

Keep out of reach of children.

If swallowed, get medical help or contact a Poison Control Center right away.

DOSAGE AND ADMINISTRATION

Directions:Twist top to open, flush the affected eye as needed, controlling the rate of flow of solution by pressure on the bottle, discard bottle after use.

Other Information:
Store out of direct sunlight between 15 degrees C and 30 degrees C (59 degrees F - 86 degrees F)

Inactive Ingredients:
Potassium phosphate monobasic, sodium chloride USP, sodium hydroxide.

PACKAGE LABEL

Salinaax
Tamper-evident ca do not use if twist-off or is broken or missing
Preservative free
Eye Wash and Skin Flush
Single Use Only
Sterile Buffered Isotonic Solution
5fl.oz (148ml)
Compliance: Ansi/isea
(As personal eye wash only)
AAXIS Excelling in healthcare solutions